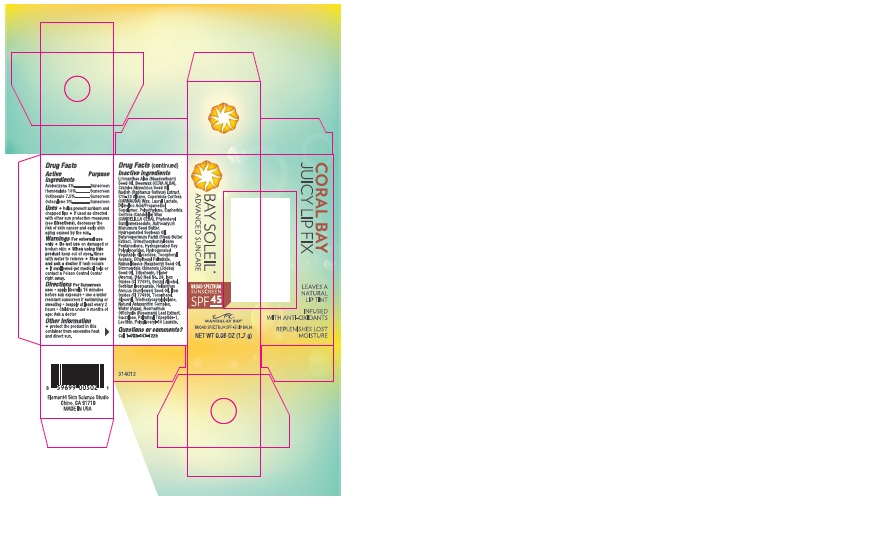 DRUG LABEL: Coral Bay Juicy Lip Fix SPF45
NDC: 61531-102 | Form: STICK
Manufacturer: Universal Packaging Systems, Inc. DBA: PakLab
Category: otc | Type: HUMAN OTC DRUG LABEL
Date: 20151116

ACTIVE INGREDIENTS: HOMOSALATE 0.1 g/1 g; OCTOCRYLENE 0.03 g/1 g; OCTINOXATE 0.075 g/1 g; AVOBENZONE 0.03 g/1 g
INACTIVE INGREDIENTS: GLYCERIN

ACTIVE INGREDIENT

Homosalate 10.00%

Octocrylene 3.00%

Octinoxate 7.50%

Avobenzone 3.00%

PURPOSE

Helps prevent sunburn and chapped lips

INSTRUCTIONS FOR USE

Apply liberally 15 minutes before sun exposure

INACTIVE INGREDIENT

Limnanthes Alba (Meadowfoam) Seed Oil, Beeswax (CERA ALBA), Crambe Abyssinica Seed Oil, Radish (Raphanus Sativus) Extract, C15-23 Alkane, Copernicia Cerifera (CARNAUBA) Wax, Lauryl Lactate, Dilinoleic Acid/Propanediol Copolymer, Polyethylene, Euphorbia Cerifera (Candelilla) Wax (CANDELILLA CERA), Phytosteryl Sunflowerseedate, Astrocaryum Murumuru Seed Butter, Hydrogenated Soybean Oil, Butyrospermum Parkii (Shea) Butter Extract, Trimethoxybenzylidene Pentanedione, Hydrogenated Soy Polyglycerides, Hydrogenated Vegetable Glycerades, Tocopheryl Acetate, Ethylhexyl Palmitate, Rubus Idaeus (Raspberry) Seed Oil, Simmondsia Chinensis (Jojoba) Seed Oil, Tribehenin, Flavor (Aroma), D&C Red No. 28, Iron Oxides (CI 77491), Benzyl Alcohol, Sorbitan Isostearate, Helianthus Annuus (Sunflower) Seed Oil, Iron Oxides (CI 77499), Tocopherol, Glycerol, Triethoxycaprylylsilane, Natural Astaxanthin Complex, Water (Aqua), Rosmarinus Officinalis (Rosemary) Leaf Extract, Sucralose, Palmitoyl Tripeptide-1, Lecithin, Polyglyceryl-10 Laurate

Questions or Comments? 1-702-347-1229

WARNINGS

For external use only. Do not use on damaged or broken skin. When using this product keep out of eyes. Rinse with water to remove. Stop use and ask a doctor if rash occurs. If swallowed get medical help ro contact a Poison Control Center right away.

INDICATIONS AND USAGE

Helps prevent sunburn and chapped lips.

DOSAGE AND ADMINISTRATION

Topical stick